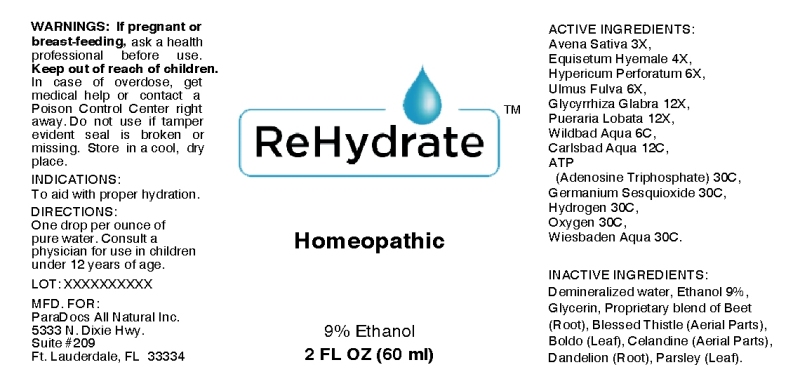 DRUG LABEL: Rehydrate
NDC: 57520-0421 | Form: LIQUID
Manufacturer: Apotheca Company
Category: homeopathic | Type: HUMAN OTC DRUG LABEL
Date: 20120120

ACTIVE INGREDIENTS: AVENA SATIVA FLOWERING TOP 3 [hp_X]/1 mL; EQUISETUM HYEMALE 4 [hp_X]/1 mL; HYPERICUM PERFORATUM 6 [hp_X]/1 mL; GLYCYRRHIZA GLABRA 12 [hp_X]/1 mL; PUERARIA MONTANA VAR. LOBATA ROOT 12 [hp_X]/1 mL; ADENOSINE TRIPHOSPHATE 30 [hp_C]/1 mL; GERMANIUM SESQUIOXIDE 30 [hp_C]/1 mL; HYDROGEN 30 [hp_C]/1 mL; OXYGEN 30 [hp_C]/1 mL; ULMUS RUBRA BARK 6 [hp_X]/1 mL; WATER 30 [hp_C]/1 mL
INACTIVE INGREDIENTS: BETA VULGARIS; CNICUS BENEDICTUS; PEUMUS BOLDUS LEAF; CHELIDONIUM MAJUS; TARAXACUM OFFICINALE; PETROSELINUM CRISPUM; GLYCERIN; ALCOHOL; WATER

Rehydrate

ACTIVE INGREDIENT

ACTIVE INGREDIENTS: Avena sativa 3X, Equisetum hyemale 4X, Hypericum perforatum 6X, Ulmus fulva 6X, Glycyrrhiza glabra 12X, Pueraria lobata 12X, Wildbad aqua 6C, Carlsbad aqua 12C, ATP (adenosine triphosphate) 30C, Germanium sesquioxide 30C, Hydrogen 30C, Oxygen 30C, Wiesbaden aqua 30C.

PURPOSE

INDICATIONS: To aid with proper hydration.

WARNINGS

WARNINGS: If pregnant or breast-feeding, ask a health care professional before use.

Keep out of reach of children. In case of overdose, get medical help or contact a Poison Control Center right away.

Do not use if tamper evident seal is broken or missing. Store in a cool, dry place.

DOSAGE AND ADMINISTRATION

DIRECTIONS: One drop per ounce of pure water. Consult a physician for use in children under 12 years of age.

INACTIVE INGREDIENT

INACTIVE INGREDIENTS: Demineralized water, Ethanol 9%, Glycerin, Proprietary blend of Beet (Root), Blessed Thistle (Aerial Parts), Boldo (Leaf), Celandine (Aerial Parts), Dandelion (Root), Parsley (Leaf).

KEEP OUT OF REACH OF CHILDREN. In case of overdose, get medical help or contact a Poison Control Center right away.

INDICATIONS: To aid with proper hydration.

QUESTIONS

MFG. FOR:

ParaDocs All Natural Inc.

5333 N. Dixie Hwy.
Suite #209
Ft. Lauderdale, FL 33334

PACKAGE LABEL

ReHydrate

Homeopathic

2 FL OZ (60 ml)